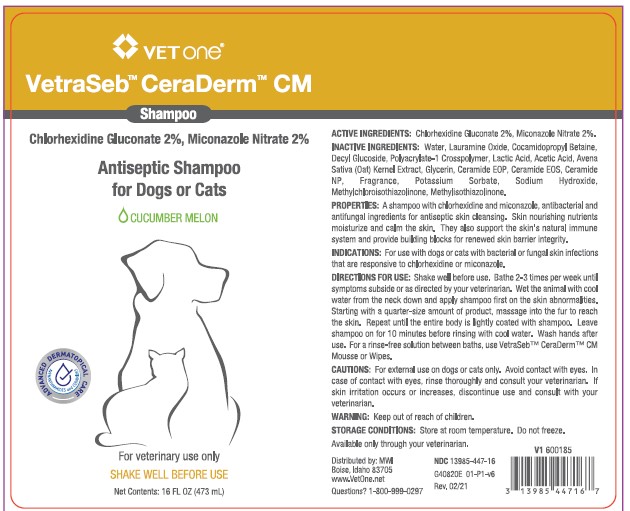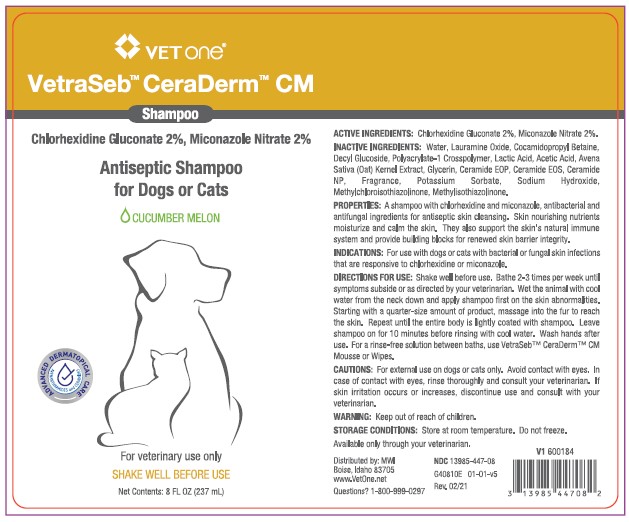 DRUG LABEL: VetraSeb CeraDerm
NDC: 13985-447 | Form: SHAMPOO
Manufacturer: MWI/VETONE
Category: animal | Type: OTC ANIMAL DRUG LABEL
Date: 20210409

ACTIVE INGREDIENTS: CHLORHEXIDINE GLUCONATE 20 mg/1 mL; MICONAZOLE NITRATE 20 mg/1 mL
INACTIVE INGREDIENTS: WATER; LAURAMINE OXIDE; COCAMIDOPROPYL BETAINE; DECYL GLUCOSIDE; CARBOMER HOMOPOLYMER, UNSPECIFIED TYPE; LACTIC ACID; ACETIC ACID; AVENANTHRAMIDES; GLYCERIN; CERAMIDE 1; CERAMIDE EOS; CERAMIDE NP; POTASSIUM SORBATE; SODIUM HYDROXIDE; METHYLCHLOROISOTHIAZOLINONE; METHYLISOTHIAZOLINONE

DESCRIPTION

VetraSeb™ CeraDerm™ CM

Antiseptic Shampoo

for Dogs or Cats

CUCUMBER MELON

ACTIVE INGREDIENTS: Chlorhexidine Gluconate 2%, Miconazole Nitrate 2%.

INACTIVE INGREDIENTS: Water, Lauramine Oxide, Cocamidopropyl Betaine, Decyl Glucoside, Polyacrylate-1 Crosspolymer, Lactic Acid, Acetic Acid, Avena Sativa (Oat) Kernel Extract, Glycerin, Ceramide EOP, Ceramide EOS, Ceramide NP, Fragrance, Potassium Sorbate, Sodium Hydroxide, Methylchloroisothiazolinone, Methylisothiazoline.

PROPERTIES: A shampoo with chlorhexidine and miconazole, antibacterial and antifungal ingredients for skin cleansing. Skin nourishing nutrients moisturize and calm the skin. They also support the skin’s natural immune system and provide building blocks for renewed skin barrier integrity.

INDICATIONS AND USAGE

INDICATIONS: For use with dogs or cats with bacterial or fungal skin infections that are responsive to chlorhexidine or miconazole.

DIRECTIONS FOR USE: Shake well before use. Bathe 2-3 times per week until symptoms subside or as directed by your veterinarian. Wet the animal with cool water from the neck down and apply shampoo first on the skin abnormalities. Starting with a quarter-size amount of product, massage into the fur to reach the skin. Repeat until the entire body is lightly coated with shampoo. Leave shampoo on for 10 minutes before rinsing with cool water. Wash hands after use. For a rinse-free solution between baths, use VetraSeb™ CeraDerm™ CM Mousse or Wipes.

WARNINGS AND PRECAUTIONS

CAUTIONS: For external use on dogs or cats only. Avoid contact with eyes. In case of contact with eyes, rinse thoroughly and consult your veterinarian. If skin irritation occurs or increases, discontinue use and consult with your veterinarian.

WARNING: Keep out of reach of children.

STORAGE AND HANDLING

STORAGE CONDITIONS: Store at room temperature. Do not freeze.

Available only through your veterinarian.

Distributed by: MWI

Boise, Idaho 83705

www.VetOne.net

QUESTIONS? 1-800-999-0297

PRINCIPAL DISPLAY PANEL - 8 OUNCE (237 mL) Bottle

VETONE®

VetrSeb™ CeraDerm™ CM

Shampoo

Chlorhexidine Gluconate 2%, Miconazole Nitrate 2%

Antiseptic Shampoo for Dogs or Cats

CUCUMBER MELON

For veterinary use only

SHAKE WELL BEFORE USING

Net Contents: 8 FL. OZ. (237 mL)

PRINCIPAL DISPLAY PANEL - 16 OUNCE (473 mL) Bottle

VETONE®

VetrSeb™ CeraDerm™ CM

Shampoo

Chlorhexidine Gluconate 2%, Miconazole Nitrate 2%

Antiseptic Shampoo for Dogs or Cats

CUCUMBER MELON

For veterinary use only

SHAKE WELL BEFORE USING

16 FL. OZ. (473 mL)